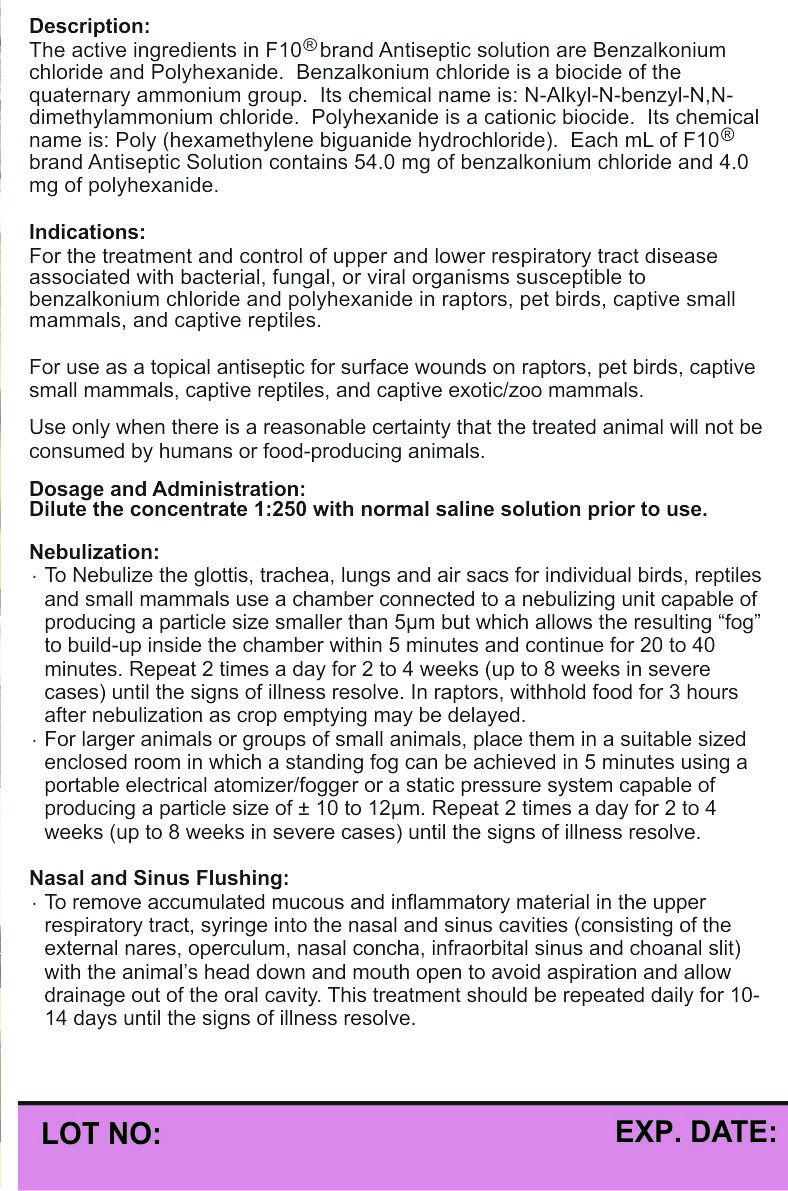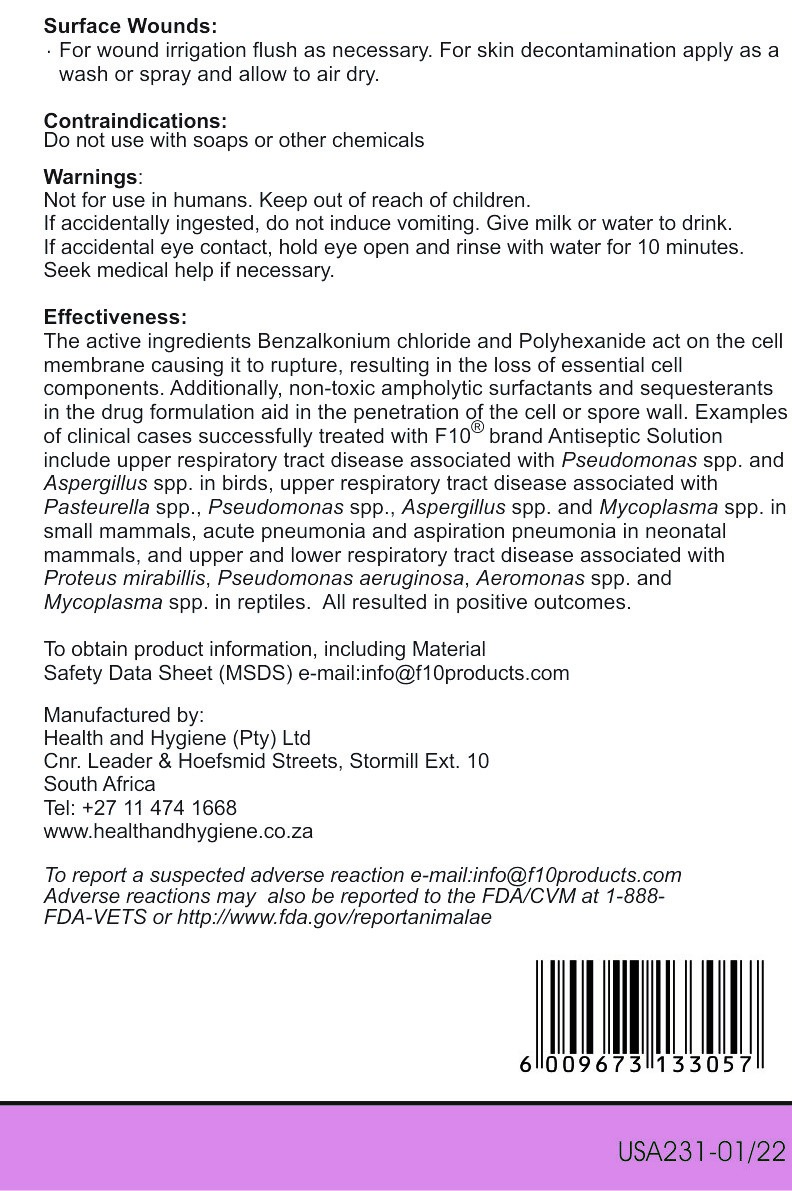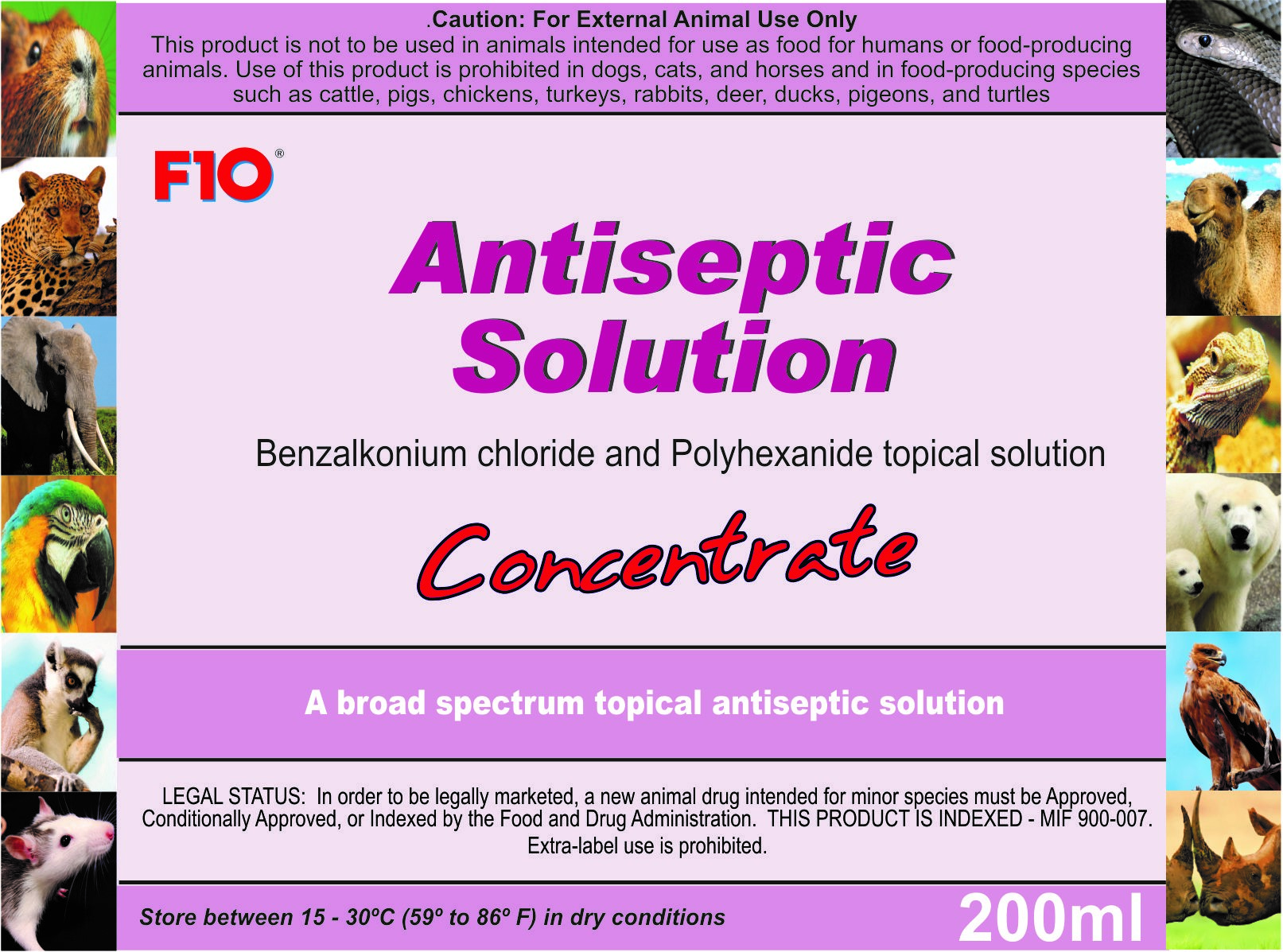 DRUG LABEL: F10
NDC: 86152-0071 | Form: LIQUID
Manufacturer: Health and Hygiene (Pty) Ltd
Category: animal | Type: PRESCRIPTION ANIMAL DRUG LABEL
Date: 20220128

ACTIVE INGREDIENTS: BENZALKONIUM CHLORIDE 5.4 g/100 mL; BIGUANIDE 0.4 g/100 mL

F10 Antiseptic Solution Concentrate

Warnings

Not for use in humans. Keep out of reach of children

Uses

For the treatment and control of upper and lower respiratory tract diseases associated with bacterial, fungal, or viral organisms.

For use as a topical antiseptic for surface wounds.

Direction of use

The concentrate need to be diluted with distilled or saline solution 1:250 prior to use.

Use for Nebulization, nasal and sinus flushing and surface wounds.

See label for further instructions

Packaging label

Front Panel

US231-01 22 ANTISEPTIC SOLUTION CONCENTRATE -200ml- GENERIC FP.jpg

Packaging Label

Back Panel

US231-01 22 ANTISEPTIC SOLUTION CONCENTRATE -200ml- GENERIC BP.jpg

Packaging Label

Back Panel 2

US231-01 22 ANTISEPTIC SOLUTION CONCENTRATE -200ml- GENERIC BP2.jpg